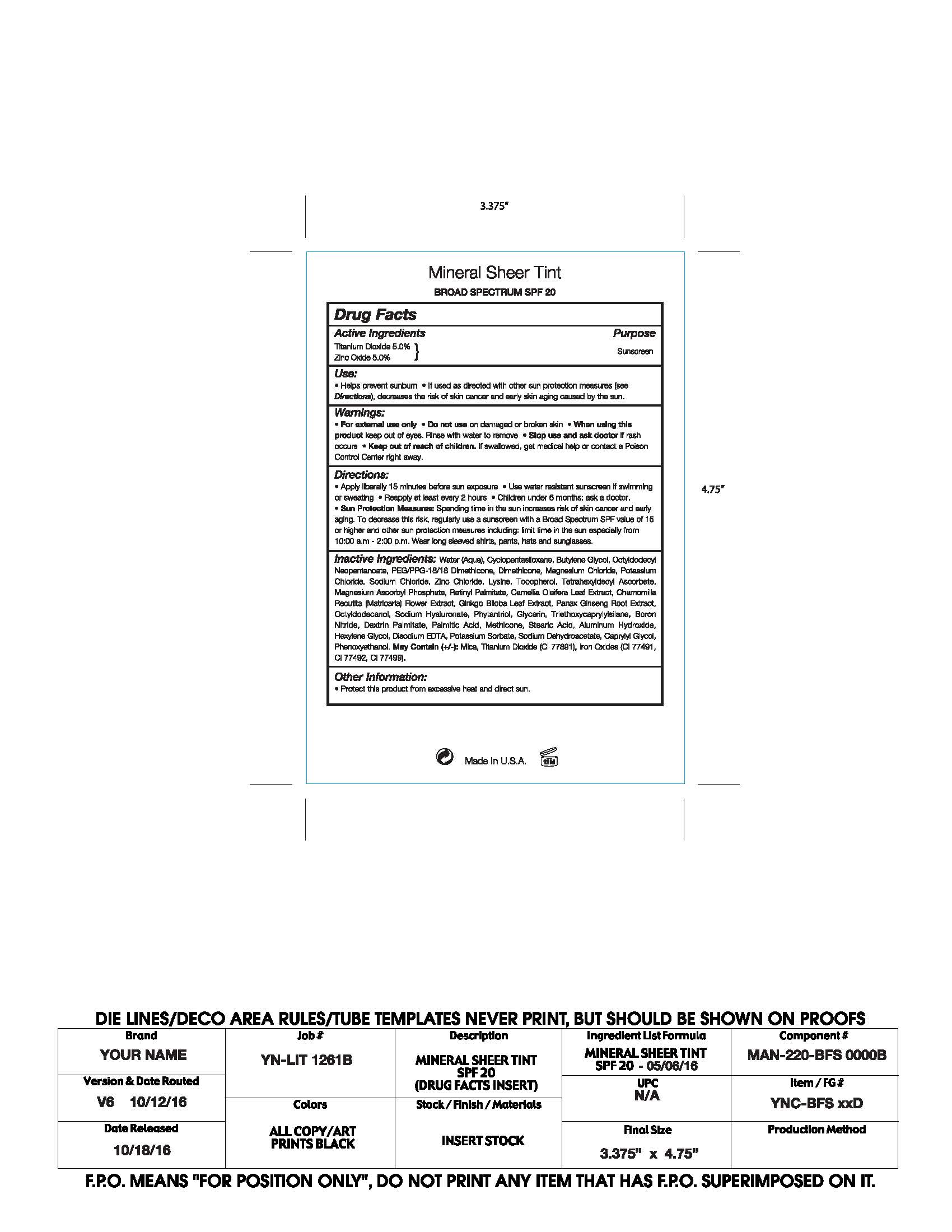 DRUG LABEL: Your Name Cosmetics Mineral Sheet Tint Broad Spectrum SPF 20
NDC: 59735-170 | Form: LOTION
Manufacturer: Mana Products
Category: otc | Type: HUMAN OTC DRUG LABEL
Date: 20180125

ACTIVE INGREDIENTS: TITANIUM DIOXIDE 5 g/100 g
INACTIVE INGREDIENTS: ZINC OXIDE; WATER; BUTYLENE GLYCOL; OCTYLDODECYL NEOPENTANOATE; PEG/PPG-18/18 DIMETHICONE; MAGNESIUM CHLORIDE; POTASSIUM CHLORIDE; SODIUM CHLORIDE; ZINC CHLORIDE; LYSINE; TOCOPHEROL; TETRAHEXYLDECYL ASCORBATE; MAGNESIUM ASCORBYL PHOSPHATE; RETINOL; CAMELLIA OLEIFERA LEAF; CAMELLIA RETICULATA WHOLE; GINKGO BILOBA LEAF OIL; PANAX GINSENG LEAF; OCTYLDODECANOL; PHYTANTRIOL; GLYCERIN; TRIETHOXYCAPRYLYLSILANE; BORON NITRIDE; DEXTRIN PALMITATE (CORN; 20000 MW); PALMITIC ACID; STEARIC ACID; ALUMINUM HYDROXIDE; HEXYLENE GLYCOL; DISODIUM EDTA-COPPER; POTASSIUM SORBATE; SODIUM DEHYDROACETATE; CAPRYLYL GLYCOL; PHENOXYETHANOL

DRUG FACTS

Active Ingredients

Titanium Dioxide 5.00%

Zinc Oxide 5.00%

Use

- Helps prevent sunburn.
- If used as directed with other sun protection measures (see Directions), decreases the risk of skin cancer and early skin aging caused by the sun.

Warnings

- For external use only
- Do not use on damaged or broken skin
- When using this product keep out of eyes. Rinse with water to remove.
- Stop use and ask a docor if rash occurs
- Keep out of reach of children. If swalled, get medical help or contact a Poison Control Center right away.

Directions

- Apply liberally 15 minutes before sun exposure
- Reapply at least every 2 hours
- Use water resistant sunscreen if swimming or sweathing
- Sun Protection Measures: Spending time in the sun decreases risk of skin cancer and early again. To decrease this risk, regulaory use a sunscreen with a Broad Spectrum SPF value of 15 or higher and other sun protection measures including: Limit time in the sun especially from 10:00 am - 2:00 pm. Wear long sleeved shirts, pants, hats and sunglasses.
- Children under 6 months: ask a doctor

Inactive Ingredients

Water (Aqua), Cyclopentasiloxane, Butylene Glycol, Octyldodecyl Neopentanoate, PEG/PPG-18/18 Dimethicone, Dimethicone, Magnesium Chloride, Potassium Chloride, Sodium Chloride, Zinc Chloride, Lysine, Tocopherol, Tetrahexyldecyl Ascorbate, Magnesium Ascorbyl Phosphate, Retinyl Palmitate, Camellia Oleifera Leaf Extract, Chamomilla Recutita (Matricaria) Flower Extract, Ginko Biloba Leaf Extract, Panax Ginsing Root Extract, Octyldodecanol, Sodium Hyaluronate, Phytantriol, Glycerin, Triethoxycaprylylsilane, Boron Nitride, Dextrin Palmitate, Palmitic Acid, Mechiecone, Stearic Acid, Aluminum Hydroxide, Hexylene Glycol, Disodium EDTA, Potassium Sorbate, Sodium Dehydroacetate, Caprylyl Glycol, Phenoxyethanol. May Contain (+/-): Mica, Iron Oxides.

Other Information

- Protect this product form excessive heat and direct sun